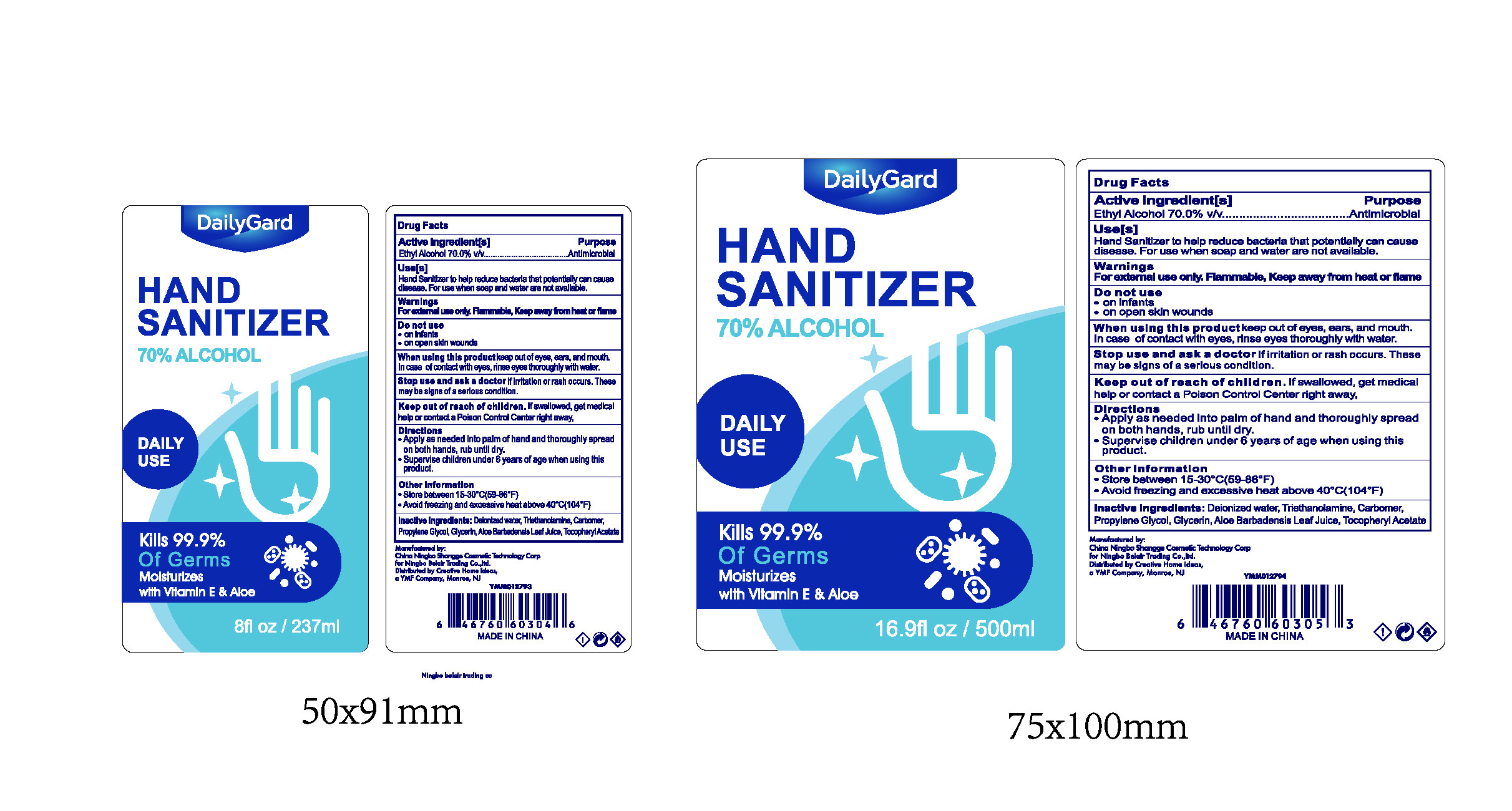 DRUG LABEL: Hand Sanitizer
NDC: 58503-802 | Form: GEL
Manufacturer: China Ningbo Shangge Cosmetic Technology Corp.
Category: otc | Type: HUMAN OTC DRUG LABEL
Date: 20200610

ACTIVE INGREDIENTS: ALCOHOL 70 mL/100 mL
INACTIVE INGREDIENTS: ALOE VERA LEAF; GLYCERIN; CARBOMER HOMOPOLYMER, UNSPECIFIED TYPE; WATER; TROLAMINE; PROPYLENE GLYCOL; .ALPHA.-TOCOPHEROL ACETATE

Hand Sanitizer

Active Ingredient(s)

Ethyl Alcohol 70.0%V/v

Purpose

Antimicrobial

Use

Hand Sanitizer to help reduce bacteria that potentially can cause disease. For use when soap and water are not avaliable.

Warnings

For extemal use only. Flammable, Keep away from heat or flame

Do not use

● on infants
● on open skin wounds

When using this product keep out of eyes, ears, and mouth.
In case of contact with eyes, rinse eyes thoroughly with water.
Stop use and ask a doctor lf irritation or rash occurs. these may be signs of a serious condition.

Stop use and ask a doctor lf irritation or rash occurs. these may be signs of a serious condition.

Keep out of reach of children. If swallowed, get medical help or contact a Poison Control Center right away,

Directions

● Apply as needed into palm of hand and thoroughly spread on both hands, rub until dry.
● Supervise children under 6 years of age when using thisproduct.

Other information

● Store between15-30°c(59-86°F)
● Avoid freezing and excessive heat above40°c(104°F)

Inactive ingredients

Deionized water, Triethanolamine, Carbomer,Propylene Glycol, Glycerin, Aloe Barbadensis Leaf Juice, Tocophe Acetate